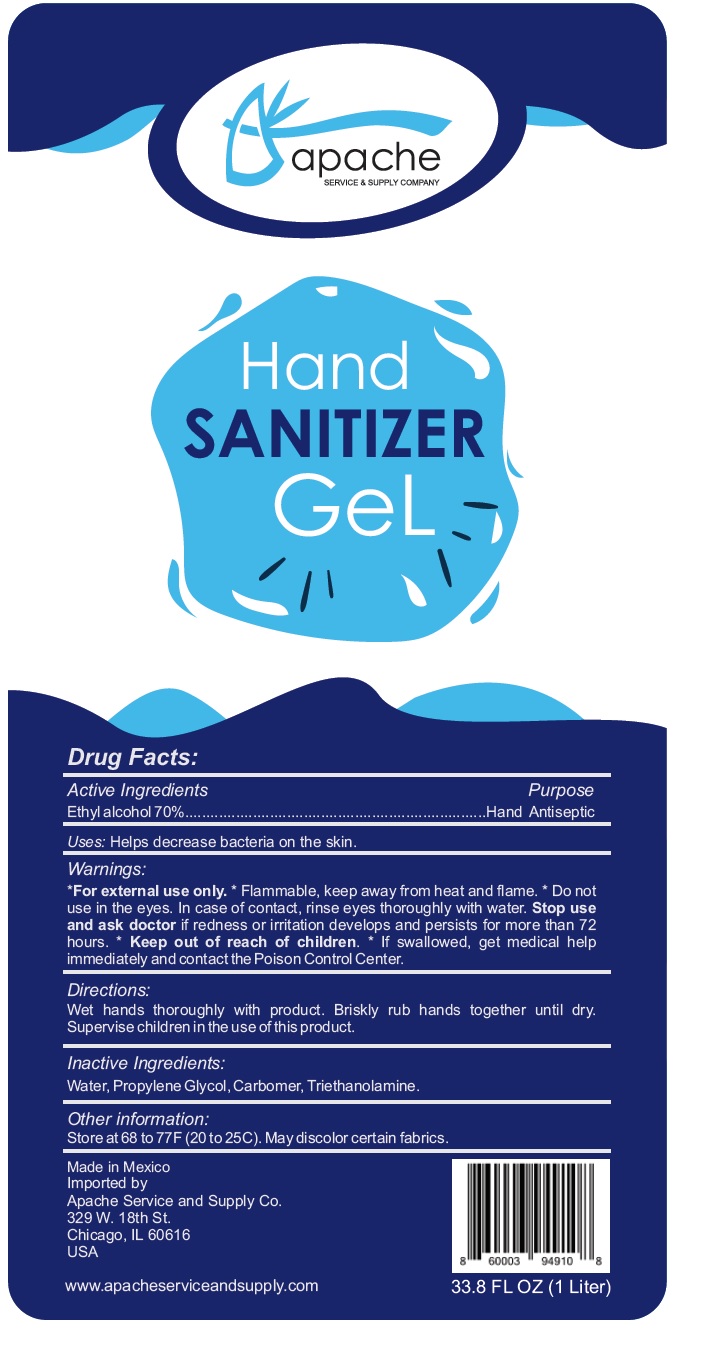 DRUG LABEL: Apache Service and Supply Company Hand Sanitizer
NDC: 79075-000 | Form: GEL
Manufacturer: Apache Service and Supply Co., Inc
Category: otc | Type: HUMAN OTC DRUG LABEL
Date: 20200717

ACTIVE INGREDIENTS: ALCOHOL 0.7 mL/1 mL
INACTIVE INGREDIENTS: CARBOMER HOMOPOLYMER, UNSPECIFIED TYPE; TROLAMINE; WATER; PROPYLENE GLYCOL

Apache Service and Supply Company Hand Sanitizer Gel

Active Ingredients

Ethyl alcohol 70%

Purpose

Hand Antiseptic

Uses:

Helps decrease bacteria on the skin.

Warnings:

*For external use only. * Flammable, keep away from heat and flame.

Do not use

* in the eyes. In case of contact, rinse eyes thoroughly with water.

Stop use and ask doctor

if redness or irritation develops and persists for more than 72 hours.

Keep out of reach of children.

* If swallowed, get medical help immediately and contact the Poison Control Center.

Directions:

Wet hands thoroughly with product. Briskly rub hands together until dry. Supervise children in the use of this product.

Inactive Ingredients:

Water, Propylene Glycol, Carbomer, Triethanolamine.

Other information:

Store at 68 to 77F (20 to 25C). May discolor certain fabrics.